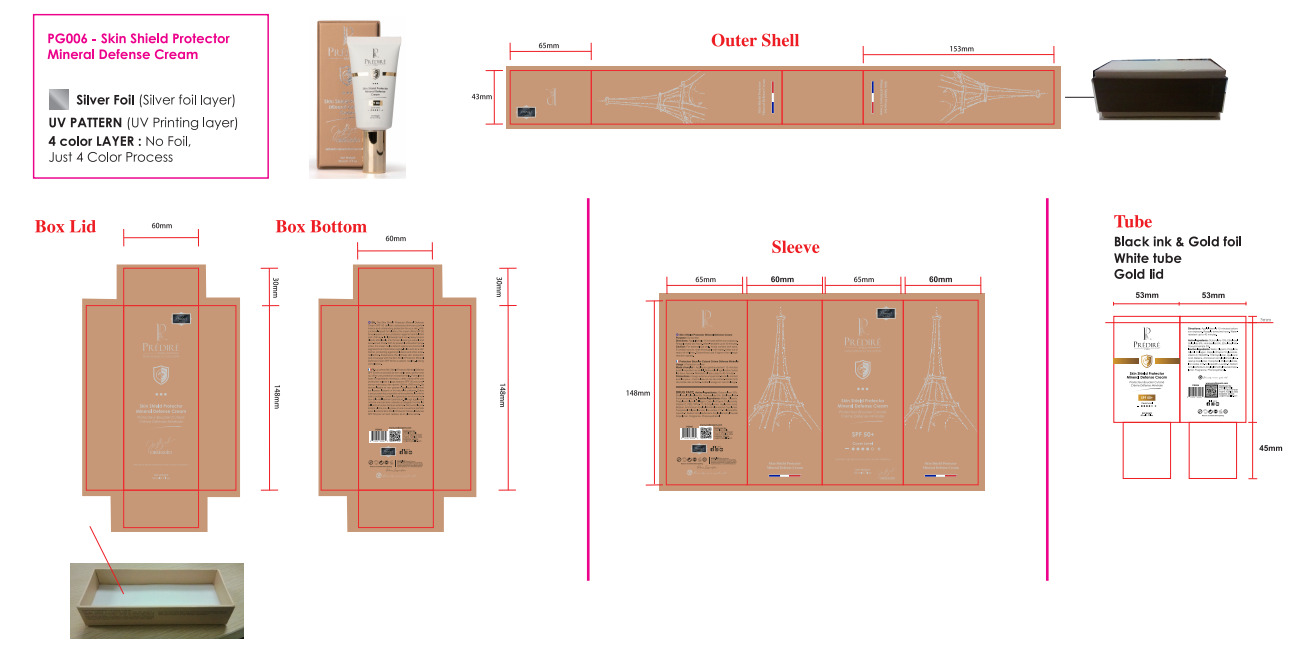 DRUG LABEL: PREDIRE PARIS skin shield protector mineral defense cream
NDC: 83447-012 | Form: CREAM
Manufacturer: Guangzhou Fantesy Biotechnology Co.,Ltd
Category: otc | Type: HUMAN OTC DRUG LABEL
Date: 20250721

ACTIVE INGREDIENTS: ETHYLHEXYL SALICYLATE 8 g/100 mL; HOMOSALATE 5 g/100 mL; ETHYLHEXYL METHOXYCINNAMATE 3 g/100 mL; OCTOCRYLENE 10 g/100 mL
INACTIVE INGREDIENTS: PEG/PPG-17/6 COPOLYMER; HYALURONIC ACID; FERROUS OXIDE; BETAINE; TOCOPHEROL; LAURETH-7; PHENOXYETHANOL; AQUA; GLYCERIN; PROPYLENE GLYCOL; COLLAGEN, SOLUBLE, FISH SKIN; CAPRYLIC/CAPRIC TRIGLYCERIDE; ASCORBIC ACID; PEACH; C13-14 ISOPARAFFIN; AMMONIUM ACRYLOYLDIMETHYLTAURATE/VP COPOLYMER; POLYACRYLAMIDE (1500 MW)

83447-012

Active ingredients

Octocrylene 10%

Ethylhexyl Salicylate 8%

Homosalate 5%

Ethylhexyl Methoxycinnamate 3%

Purpose

Sunscreen

Uses

Helps prevent sunburn
If used as directed with other sun protection measures (see Directions), decreases the risk of skin cancer and early skin aging caused by the sun

Warnings

For external use only.

Do not use on damaged or broken skin.

When using this product, keep out of eyes. Rinse with water to remove.

Stop use

Stop use and ask a doctor if rash occurs.

Keep out of reach of children . If product is swallowed . get medical help or contact a Poison Control Center right away.

Directions

Apply liberally 15 minutes before sun exposure. Reapply every two hours. Water-
resistant up to 40 minutes.

Other information

Store at room temperature

Inactive ingredients

Water, Glycerin, Propylene Glycol, Collagen, Caprylic/Capric Triglyceride,
Vitamin C, PEG/PPG- 17 / 6 Copolymer, Hyaluronic Acid,
Betaine, Ammonium Acryloyldimethyltaurate/vp Copolymer,
Tocopherol, Polyacrylamide, lron oxides, C13- 14 Isoparaffin,
Laureth-7, Sodium Acrylate/Sodium Acryloyldimethyl Taurate
Copolymer, Fragrance, Phenoxyethanol.